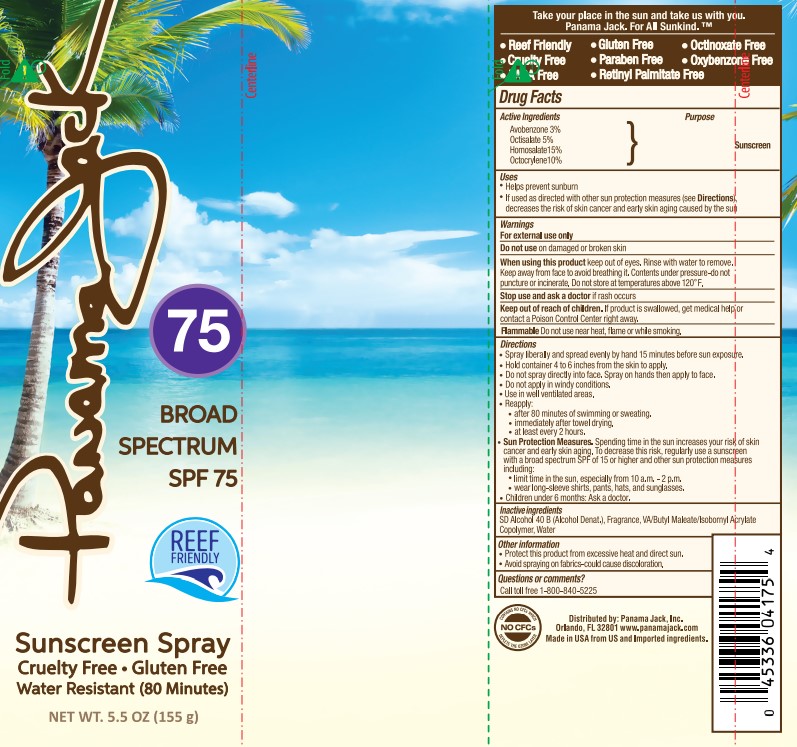 DRUG LABEL: Pamana Jack
NDC: 13630-0250 | Form: SPRAY
Manufacturer: Prime Packaging, Inc.
Category: otc | Type: HUMAN OTC DRUG LABEL
Date: 20220909

ACTIVE INGREDIENTS: AVOBENZONE 25.89 mg/1 mL; OCTISALATE 43.15 mg/1 mL; OCTOCRYLENE 86.3 mg/1 mL; HOMOSALATE 129.45 mg/1 mL
INACTIVE INGREDIENTS: ALCOHOL; WATER

Panama Jack Broad Spectrum SPF 75 Sunscreen Spray

Active Ingredients

Avobenzone 3%

Octisalate 5%

Homosalate 15%

Octocrylene 10%

Purpose

Sunscreen

Uses

- Helps prevent sunburn
- If used as directed with other sun protection measures (see Directions), decreases the risk of skin cancer and early skin aging caused by the sun

Warnings

For external use only

Do not use on damaged or broken skin

When using this product keep out of eyes. Rinse with water to remove. Keep away from face to avoid breathing it. Contents under pressure - do not puncture or incinerate. Do not store at temperatures above 120°F.

Stop use and ask a doctor if rash occurs

Keep out of reach of children. If product is swallowed, get medical help or contact a Poison Control Center right away.

Flammable Do not use near heat, flame or while smoking.

Directions

- Spray liberally and spray evenly by hand 15 minutes before sun exposure.
- Hold container 4 to 6 inches from the skin to apply.
- Do not spray directly into face. Spray on hands then apply to face.
- Do not apply in windy conditions.
- Use in well ventilated areas.
- Reapply:
- after 80 minutes of swimming or sweating.
- immediately after towel drying.
- at least every 2 hours.
- Sun Protection Measures. Spending time in the sun increases your risk of skin cancer and early skin aging. To decrease this risk, regularly use a sunscreen with a broad spectrum SPF of 15 or higher and other sun protection measures including:
- limit time in the sun, especially from 10 a.m. – 2 p.m.
- wear long-sleeve shirts, pants, hats, and sunglasses
- Children under 6 months: Ask a doctor

Inactive ingredients

SD Alcohol 40-B, Fragrance, VA/Butyl Maleate/Isobornyl Acrylate Copolymer, Water

Other information

- Protect this product from excessive heat and direct sun.
- Avoid spraying on fabrics-could cause discoloration.

Questions or comments?

Call toll free 1-800-840-5225